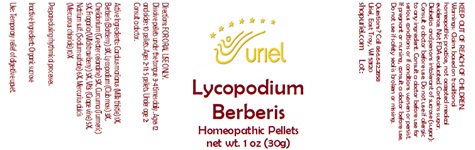 DRUG LABEL: Lycopodium Berberis
NDC: 48951-6049 | Form: PELLET
Manufacturer: Uriel Pharmacy Inc.
Category: homeopathic | Type: HUMAN OTC DRUG LABEL
Date: 20251030

ACTIVE INGREDIENTS: MILK THISTLE 1 [hp_X]/1 1; BERBERIS VULGARIS ROOT BARK 3 [hp_X]/1 1; LYCOPODIUM CLAVATUM SPORE 3 [hp_X]/1 1; CHELIDONIUM MAJUS ROOT 5 [hp_X]/1 1; TURMERIC 5 [hp_X]/1 1; FRAGARIA VESCA WHOLE 5 [hp_X]/1 1; VITIS VINIFERA LEAF 5 [hp_X]/1 1; SULFIDE ION 6 [hp_X]/1 1; CALOMEL 10 [hp_X]/1 1
INACTIVE INGREDIENTS: SUCROSE

Lycopodium Berberis

INDICATIONS AND USAGE

Directions: FOR ORAL USE ONLY.

DOSAGE AND ADMINISTRATION

Dissolve pellets under the tongue 3-4 times daily. Ages 12 and older: 10 pellets. Ages 2-11: 5 pellets. Under age 2: Consult a doctor.

ACTIVE INGREDIENT

Active Ingredients: Carduus marianus (Milk thistle) 1X, Berberis (Barberry) 3X, Lycopodium (Club moss) 3X, Chelidonium (Greater celandine) 5X, Curcuma (Turmeric) 5X, Fragaria (Wild strawberry) 5X, Vitis (Grape vine) 5X, Natrium sulf. (Sodium sulfate) 6X, Mercurius dulcis (Mercurous chloride) 10X

INACTIVE INGREDIENT

Prepared using rhythmical processes.

Inactive Ingredient: Organic sucrose

PURPOSE

Use: Temporary relief of digestive upset.

KEEP OUT OF REACH OF CHILDREN.

WARNINGS

Warnings: Claims based on traditional homeopathic practice, not accepted medical evidence. Not FDA evaluated. Contains sugar. Diabetics and persons intolerant of sucrose (sugar): Consult a doctor before use. Do not use if allergic to any ingredient. Consult a doctor before use for serious conditions or if conditions worsen or persist. If pregnant or nursing, consult a doctor before use. Do not use if safety seal is broken or missing.

Questions? Call 866.642.2858
Uriel, East Troy, WI 53120
shopuriel.com Lot: